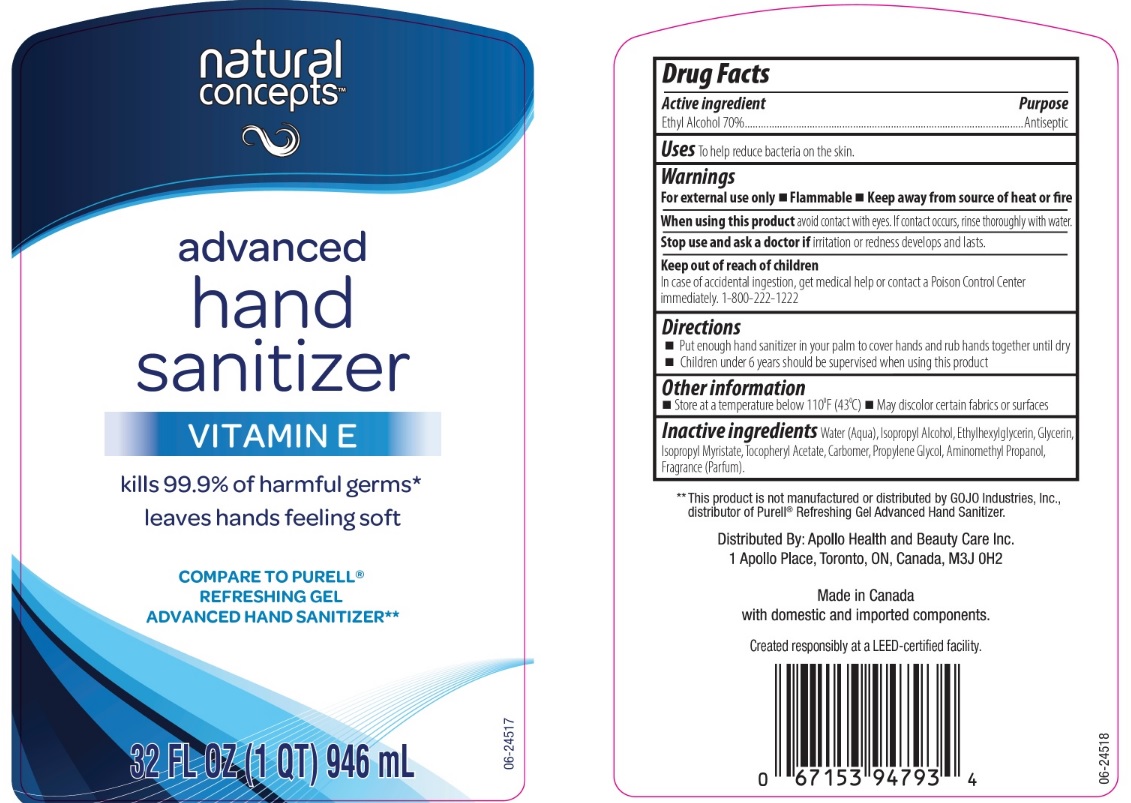 DRUG LABEL: Natural Concepts Advanced Hand Sanitizer
NDC: 63148-511 | Form: GEL
Manufacturer: Apollo Health and Beauty Care Inc.
Category: otc | Type: HUMAN OTC DRUG LABEL
Date: 20200318

ACTIVE INGREDIENTS: ALCOHOL 700 mg/1 mL
INACTIVE INGREDIENTS: WATER; ISOPROPYL ALCOHOL; ETHYLHEXYLGLYCERIN; GLYCERIN; ISOPROPYL MYRISTATE; .ALPHA.-TOCOPHEROL ACETATE, DL-; CARBOMER 934; PROPYLENE GLYCOL; AMINOMETHYLPROPANOL

Drug Facts

Active ingredient

Ethyl Alcohol 70%

Purpose

Antiseptic

Uses

to help reduce bacteria on the skin.

Warnings

For external use only

- flammable
- keep away from source of heat or fire

When using this product

avoid contact with eyes. If contact occurs, rinse thoroughly with water.

Stop use and ask a doctor if

irritation or redness develops and lasts.

Keep out of reach of children.

In case of accidental ingestion, get medical help or contact a Poison Control Center immediately. 1-800-222-1222

Directions

- put enough hand sanitizer in your palm to cover hands and rub hands together until dry.
- children under 6 years should be supervised when using this product.

Other information

- store at temperature below 110°F (43°C)
- may discolor certain fabrics or surfaces

Inactive ingredients

Water (Aqua), Isopropyl Alcohol, Ethylhexylglycerin, Glycerin, Isopropyl Myristate, Tocopheryl Acetate, Carbomer, Propylene Glycol, Aminomethyl Propanol, Fragrance (Parfum).